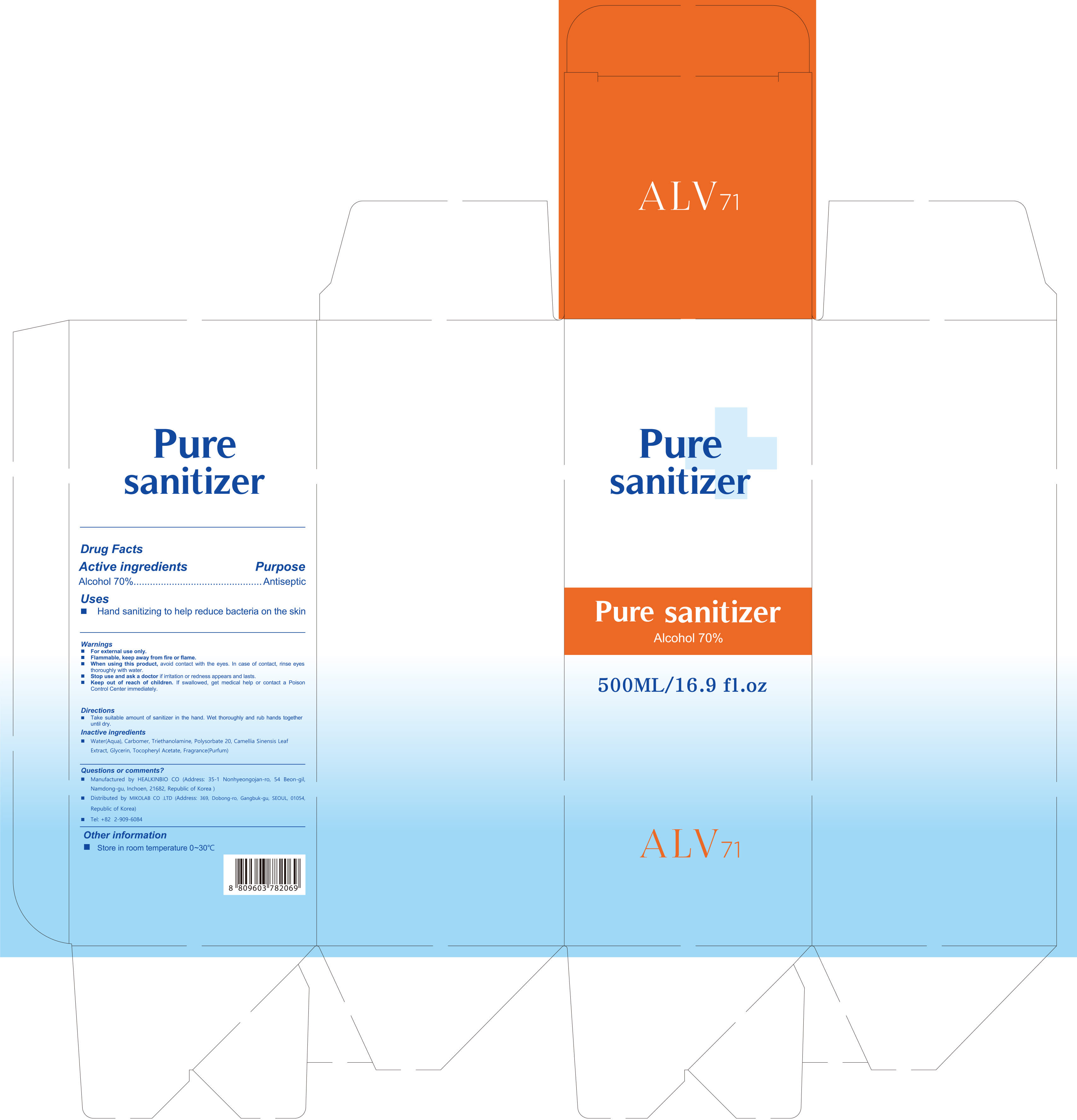 DRUG LABEL: ALV71 PURE SANITIZER 500ml
NDC: 76886-003 | Form: Gel
Manufacturer: MIKOLAB CO .LTD
Category: otc | Type: HUMAN OTC DRUG LABEL
Date: 20200429

ACTIVE INGREDIENTS: alcohol 70 mL/100 mL
INACTIVE INGREDIENTS: Water; Polysorbate 20; Glycerin

Active Ingredient(s)

Alcohol 70%

Purpose

Purpose: Antiseptic

Use

 Hand sanitizing to help reduce bacteria on the skin

Warnings

 For external use only.
 Flammable, keep away from fire or flame.
 When using this product, avoid contact with the eyes. In case of contact, rinse eyes thoroughly with water.
 Stop use and ask a doctor if irritation or redness appears and lasts.

 Keep out of reach of children. If swallowed, get medical help or contact a Poison Control Center immediately.

Directions

 Take suitable amount of sanitizer in the hand. Wet thoroughly and rub hands together until dry

Other information

 Store in room temperature 0~30℃

Inactive ingredients

 Water(Aqua), Carbomer, Triethanolamine, Polysorbate 20, Camellia Sinensis Leaf Extract, Glycerin, Tocopheryl Acetate, Fragrance(Parfum)